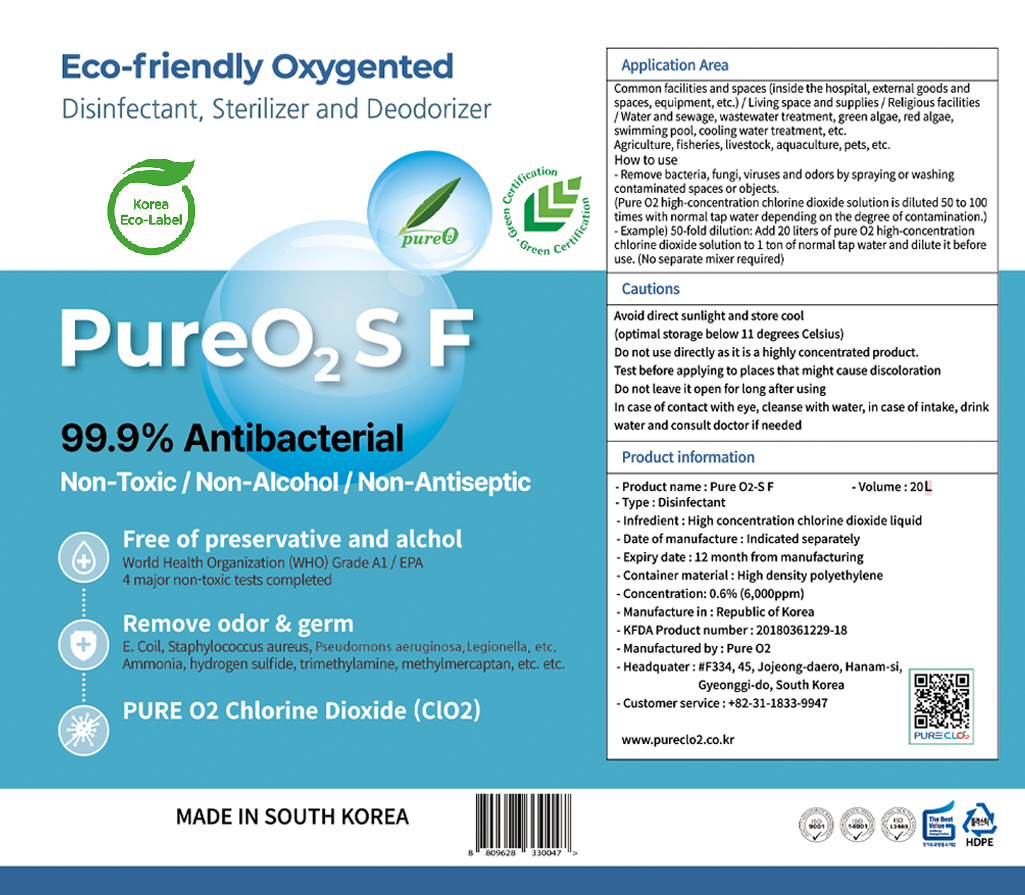 DRUG LABEL: PURE O2-S F
NDC: 75124-0014 | Form: LIQUID
Manufacturer: Pure O2
Category: otc | Type: HUMAN OTC DRUG LABEL
Date: 20250428

ACTIVE INGREDIENTS: CHLORINE DIOXIDE 0.6 g/100 mL
INACTIVE INGREDIENTS: WATER

Drug Facts

ACTIVE INGREDIENT

chlorine dioxide

INACTIVE INGREDIENT

water

PURPOSE

disinfectant, sterilizer, and deodorizer

KEEP OUT OF REACH OF THE CHILDREN

INDICATIONS AND USAGE

please see the label attached

WARNINGS

■ For external use only.

■ Do not use in eyes.

■ lf swallowed, get medical help promptly.

■ Stop use, ask doctor lf irritation occurs.

■ Keep out of reach of children.

DOSAGE AND ADMINISTRATION

for external use only